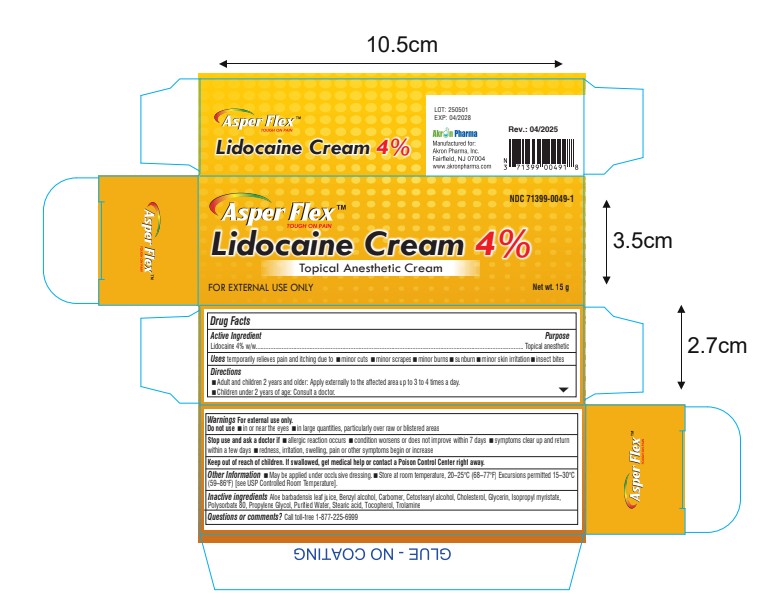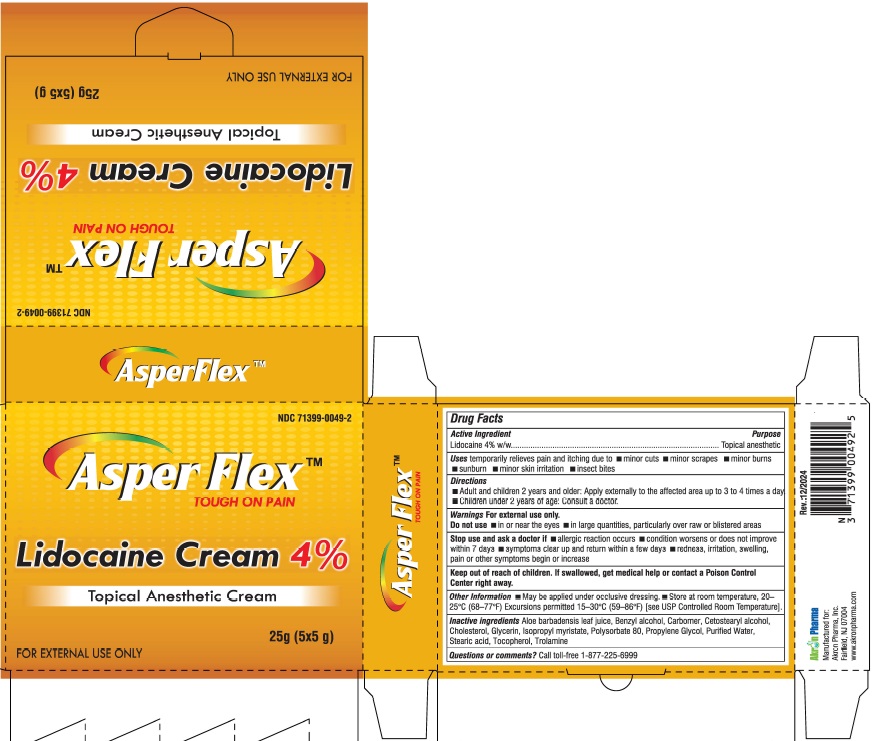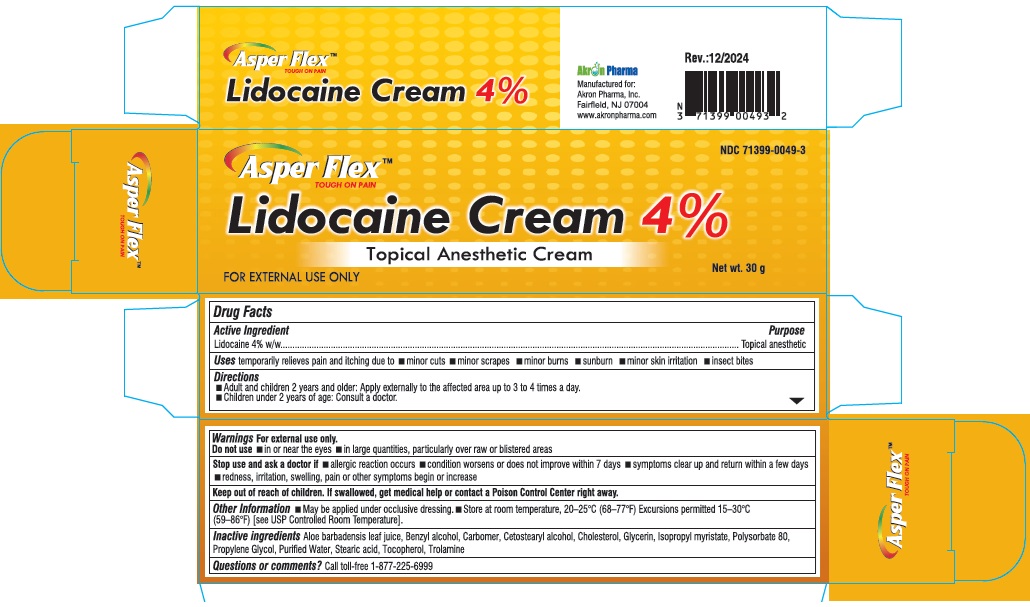 DRUG LABEL: Asper Flex
NDC: 71399-0049 | Form: CREAM
Manufacturer: Akron Pharma Inc.
Category: otc | Type: HUMAN OTC DRUG LABEL
Date: 20250919

ACTIVE INGREDIENTS: LIDOCAINE 4 g/100 g
INACTIVE INGREDIENTS: ALOE BARBADENSIS LEAF; BENZYL ALCOHOL; CARBOMER; CETOSTEARYL ALCOHOL; CHOLESTEROL; GLYCERIN; ISOPROPYL MYRISTATE; POLYSORBATE 80; PROPYLENE GLYCOL; WATER; STEARIC ACID; TOCOPHEROL; TROLAMINE

Asper Flex (Lidocaine 4% Cream)
TOUGH ON PAIN
Topical Anesthetic Cream
FOR EXTERNAL USE ONLY

Active ingredient

Lidocaine 4% w/w

Purpose

Topical anesthetic

Uses

temporarily relieves pain and itching due to

- minor cuts
- minor scrapes
- minor burns
- sunburn
- minor skin irritation
- insect bites

Warnings

For external use only

Do not use

- if you are allergice to any active or inactive ingredients of this product
- on wonds or damaged, irritated, or sensitive skin
- with any other topical anesthetic
- for more than one week without constulting a doctor
- over large areas of the body

Directions

- Adult and children 2 years and older: Apply externally to the affected area up to 3 to 4 times a day.
- Children under 2 years of age: Consult a doctor.

For external use only

Do not use

- in or near the eyes
- in large quantities, particularly over raw or blistered areas

Stop use and ask a doctor if

- allergic reaction occurs
- condition worsens or does not improve within 7 days
- symptoms clear up and return within a few days
- redness, irritation, swelling, pain or other symptoms begin or increase

Other information

- May be applied under occlusive dressing.
- Store at room temperature, 20–25°C (68–77°F) Excursions permitted 15–30°C (59–86°F) [see USP Controlled Room Temperature].

Inactive ingredients

Aloe barbadensis leaf juice, Benzyl alcohol, Carbomer, Cetostearyl alcohol, Cholesterol, Glycerin, lsopropyl myristate, Polysorbate 80, Propylene Glycol, Purified Water, Stearic acid, Tocopherol, Trolamine

Questions or comments?

Call toll-free 1-877-255-6999

Manufactured for:

Akron Pharma Inc.

Fairfield, NJ 07004

www.akronpharma.com